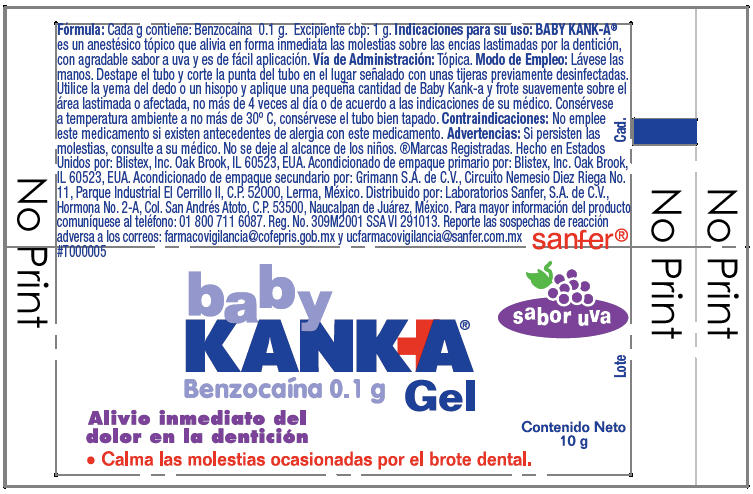 DRUG LABEL: Blistex Baby Kanka
NDC: 10157-9409 | Form: GEL
Manufacturer: Blistex Inc.
Category: otc | Type: HUMAN OTC DRUG LABEL
Date: 20150122

ACTIVE INGREDIENTS: Benzocaine 10 g/100 g
INACTIVE INGREDIENTS: POLYETHYLENE GLYCOL 400; POLYETHYLENE GLYCOL 3350; GLYCERIN; SUCRALOSE; METHYLPARABEN; PROPYLPARABEN; SORBIC ACID

Blistex Baby Kanka® Gel

Fórmula

PURPOSE

INACTIVE INGREDIENT

Cada g contiene: Benzocaína 0.1 g. Excipiente cbp: 1 g.

Indicaciones para su uso

BABY KANK-A®es un anestésico tópico que alivia en forma inmediata las molestias sobre las encías lastimadas por la dentición, con agradable sabor a uva y es de fácil aplicación.

Vía de Administración

Tópica.

Modo de Empleo

Lávese las manos. Destape el tubo y corte la punta del tubo en el lugar señalado con unas tijeras previamente desinfectadas. Utilice la yema del dedo o un hisopo y aplique una pequeña cantidad de Baby Kank-a y frote suavemente sobre el área lastimada o afectada, no más de 4 veces al día o de acuerdo a las indicaciones de su médico.

STORAGE AND HANDLING

Consérvese a temperatura ambiente a no más de 30º C, consérvese el tubo bien tapado.

Contraindicaciones

No emplee este medicamento si existen antecedentes de alergia con este medicamento.

Advertencias

ASK DOCTOR

Si persisten las molestias, consulte a su médico.

KEEP OUT OF REACH OF CHILDREN

No se deje al alcance de los niños.

Distribuido por: Laboratorios Sanfer, S.A. de C.V., Hormona No. 2-A, Col. San Andrés Atoto, C.P. 53500, Naucalpan de Juárez, México.

QUESTIONS

Para mayor información del producto comuníquese al teléfono: 01 800 711 6087. Reg. No. 309M2001 SSA VI 291013. Reporte las sospechas de reacción adversa a los correos: farmacovigilancia@cofepris.gob.mx y ucfarmacovigilancia@sanfer.com.mx

PRINCIPAL DISPLAY PANEL - 10 g Tube Label

#T000005

baby
KANKA®
Benzocaína 0.1 g Gel

sabor uva

Alivio inmediato del
dolor en la dentición

• Calma las molestias ocasionadas por el brote dental.

Contenido Neto
10 g

Lote